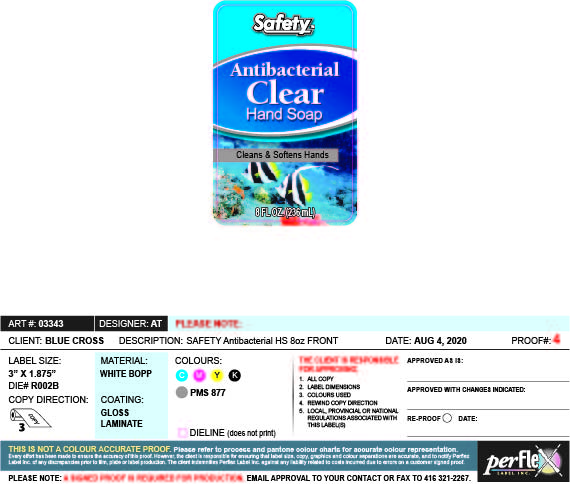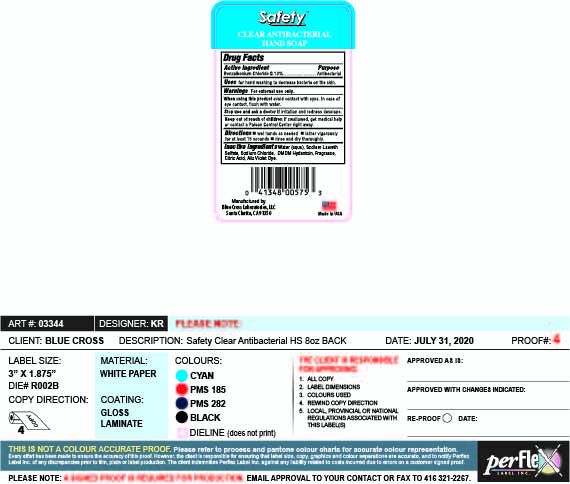 DRUG LABEL: Safety Clear Antibacterial Hand
NDC: 22431-587 | Form: LIQUID
Manufacturer: Blue Cross Laboratories, Inc
Category: otc | Type: HUMAN OTC DRUG LABEL
Date: 20200826

ACTIVE INGREDIENTS: BENZALKONIUM CHLORIDE 0.13 g/100 mL
INACTIVE INGREDIENTS: CITRIC ACID MONOHYDRATE; SODIUM CHLORIDE; DMDM HYDANTOIN; WATER; SODIUM LAURETH SULFATE

Safety Clear Antibacterial Hand

Active Ingredient Purpose

Benzalkonium Chloride 0.13% Antibacterial

PURPOSE

Uses For hand washing to decrease bacteria on the skin

Keep out of reach of children. If Swallowed, get medical help or contact a Poison Control Center.

Warnings :

For external use only

when using this product

- Avoid contact with eyes. If case of eye contact, flush with water

Stop use and ask a doctor if irritation and redness develops.

Directions

Wet hands as needed
Lather vigorously for at least 15 seconds
Wash skin, rinse and dry thoroughly

INACTIVE INGREDIENT

Inactive ingredients Water(aqua), Sodium Laureth Sulfate, Sodium Chloride, DMDM Hydantoin, Fragrance, Citric Acid, Aliz Violet Dye

PACKAGE LABEL

Safety Antibacterial

Clear

Hand Soap

Cleans & Softens Hands

8 FL OZ (236 mL)